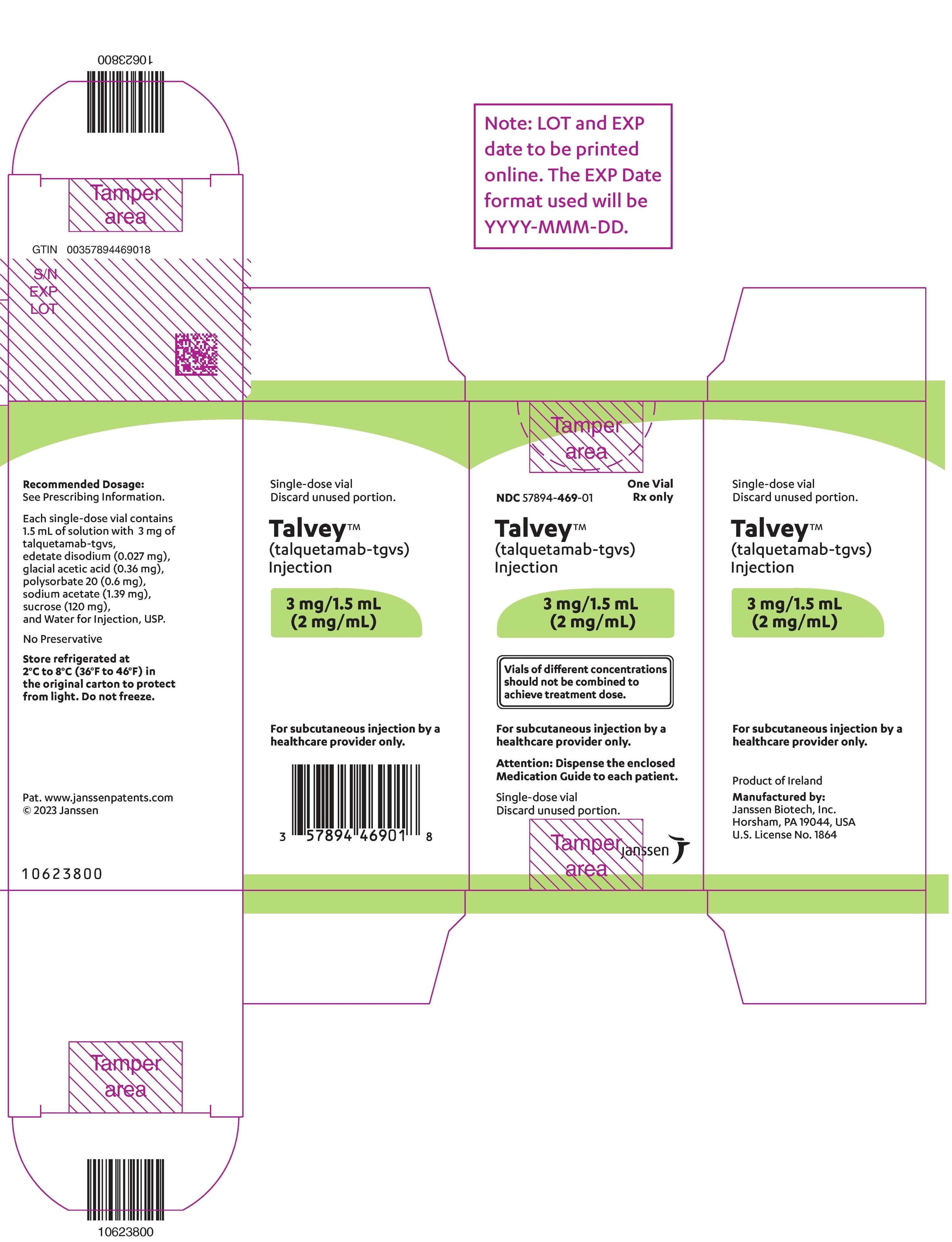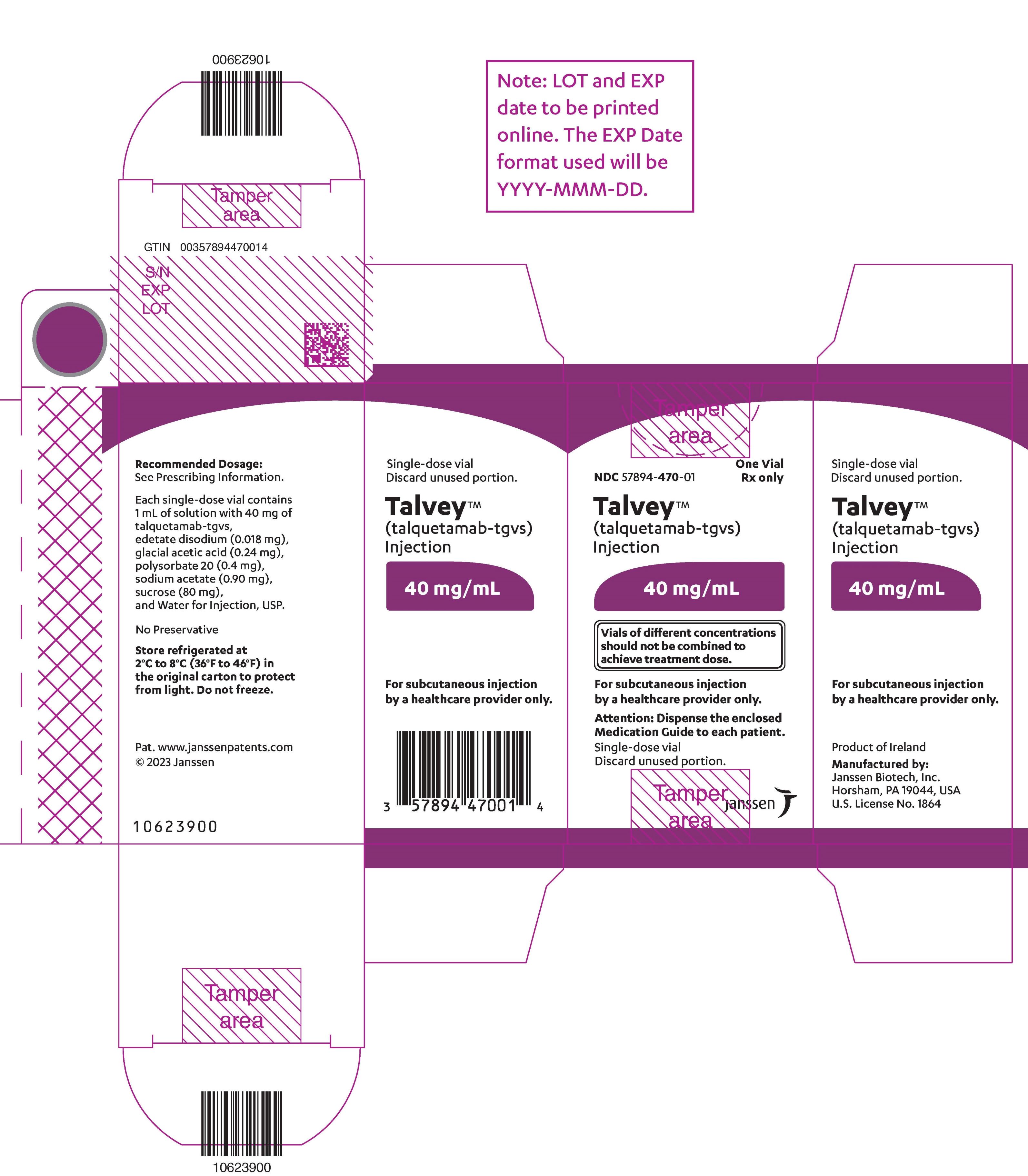 DRUG LABEL: TALVEY
NDC: 57894-469 | Form: INJECTION
Manufacturer: Janssen Biotech, Inc.
Category: prescription | Type: HUMAN PRESCRIPTION DRUG LABEL
Date: 20251008

ACTIVE INGREDIENTS: TALQUETAMAB 3 mg/1.5 mL
INACTIVE INGREDIENTS: EDETATE DISODIUM; ACETIC ACID; SUCROSE; POLYSORBATE 20; SODIUM ACETATE; WATER

HIGHLIGHTS OF PRESCRIBING INFORMATION

These highlights do not include all the information needed to use TALVEY safely and effectively. See full prescribing information for TALVEY.
TALVEY®(talquetamab-tgvs) injection, for subcutaneous use
Initial U.S. Approval: 2023

WARNING: CYTOKINE RELEASE SYNDROME and NEUROLOGIC TOXICITY, including IMMUNE EFFECTOR CELL-ASSOCIATED NEUROTOXICITY SYNDROME

See full prescribing information for complete boxed warning.

Cytokine release syndrome (CRS), including life-threatening or fatal reactions, can occur in patients receiving TALVEY. Initiate TALVEY treatment with step-up dosing to reduce the risk of CRS. Withhold TALVEY until CRS resolves or permanently discontinue based on severity. (2.2, 2.5, 5.1)

Neurologic toxicity, including immune effector cell-associated neurotoxicity syndrome (ICANS), and serious and life-threatening or fatal reactions, can occur in patients receiving TALVEY. Monitor patients for signs or symptoms of neurologic toxicity, including ICANS, during treatment. Withhold or permanently discontinue TALVEY based on severity. (2.5, 5.2)

TALVEY is available only through a restricted program called the TECVAYLI and TALVEY Risk Evaluation and Mitigation Strategy (REMS). (5.3)

RECENT MAJOR CHANGES

Dosage and Administration (2.5) | 10/2025
Warnings and Precautions (5.2) | 10/2025

1 INDICATIONS AND USAGE

TALVEY is a bispecific GPRC5D-directed CD3 T-cell engager indicated for the treatment of adult patients with relapsed or refractory multiple myeloma who have received at least four prior lines of therapy, including a proteasome inhibitor, an immunomodulatory agent and an anti-CD38 monoclonal antibody.

This indication is approved under accelerated approval based on response rate and durability of response. Continued approval for this indication may be contingent upon verification and description of clinical benefit in a confirmatory trial(s). (1)

2 DOSAGE AND ADMINISTRATION

- For subcutaneous injection. (2.2)
- Patients should be hospitalized for 48 hours after all doses within the step-up dosing schedule. (2.1)
- Administer pretreatment medications as recommended. (2.3)
- See Full Prescribing Information for instructions on preparation and administration. (2.6)

TALVEY Weekly Dosing Schedule (2.2)
Dosing schedule | Day | Dose [Based on actual body weight.]
Step-up dosing schedule | Day 1 | Step-up dose 1 | 0.01 mg/kg
Step-up dosing schedule | Day 4 [Dose may be administered between 2 to 4 days after the previous dose and may be given up to 7 days after the previous dose to allow for resolution of adverse reactions.] | Step-up dose 2 | 0.06 mg/kg
Step-up dosing schedule | Day 7 | First treatment dose | 0.4 mg/kg
Weekly dosing schedule | One week after first treatment dose and weekly thereafter [Maintain a minimum of 6 days between weekly doses.] | Subsequent treatment doses | 0.4 mg/kg once weekly

TALVEY Biweekly (Every 2 Weeks) Dosing Schedule (2.2)
Dosing schedule | Day | Dose [Based on actual body weight.]
Step-up dosing schedule | Day 1 | Step-up dose 1 | 0.01 mg/kg
Step-up dosing schedule | Day 4 [Dose may be administered between 2 to 4 days after the previous dose and may be given up to 7 days after the previous dose to allow for resolution of adverse reactions.] | Step-up dose 2 | 0.06 mg/kg
Step-up dosing schedule | Day 7 | Step-up dose 3 | 0.4 mg/kg
Step-up dosing schedule | Day 10 [Dose may be administered between 2 to 7 days after step-up dose 3.] | First treatment dose | 0.8 mg/kg
Biweekly (every 2 weeks) dosing schedule | Two weeks after first treatment dose and every 2 weeks thereafter [Maintain a minimum of 12 days between biweekly (every 2 weeks) doses.] | Subsequent treatment doses | 0.8 mg/kg every 2 weeks

3 DOSAGE FORMS AND STRENGTHS

Injection

- 3 mg/1.5 mL (2 mg/mL) in a single-dose vial (3)
- 40 mg/mL in a single-dose vial (3)

4 CONTRAINDICATIONS

None. (4)

5 WARNINGS AND PRECAUTIONS

- Oral Toxicity and Weight Loss: Monitor for oral toxicity and weight loss. Withhold or permanently discontinue based on severity. (5.4)
- Infections: Can cause serious, life-threatening, or fatal infections. Monitor for signs and symptoms of infection; treat appropriately. Withhold or consider permanent discontinuation based on severity. (5.5)
- Cytopenias: Monitor complete blood counts. (5.6)
- Skin Toxicity: Monitor for skin toxicity, including rash progression, for early intervention and treat appropriately. Withhold as recommended based on severity. (5.7)
- Hepatotoxicity:Monitor liver enzymes and bilirubin at baseline and during treatment as clinically indicated. Withhold or consider permanent discontinuation based on severity. (5.8)
- Embryo-Fetal Toxicity: May cause fetal harm. Advise females of reproductive potential of the potential risk to the fetus and to use effective contraception. (5.9, 8.1, 8.3)

6 ADVERSE REACTIONS

The most common adverse reactions (≥20%) are pyrexia, CRS, dysgeusia, nail disorder, musculoskeletal pain, skin disorder, rash, fatigue, weight decreased, dry mouth, xerosis, dysphagia, upper respiratory tract infection, diarrhea, hypotension, and headache. (6.1)

The most common Grade 3 or 4 laboratory abnormalities (≥30%) are lymphocyte count decreased, neutrophil count decreased, white blood cell decreased, and hemoglobin decreased. (6.1)

To report SUSPECTED ADVERSE REACTIONS, contact Janssen Biotech, Inc. at 1-800-JANSSEN (1-800-526-7736) or FDA at 1-800-FDA-1088 or www.fda.gov/medwatch.

8 USE IN SPECIFIC POPULATIONS

Lactation: Advise not to breastfeed. (8.2)

FULL PRESCRIBING INFORMATION

WARNING: CYTOKINE RELEASE SYNDROME and NEUROLOGIC TOXICITY, including IMMUNE EFFECTOR CELL-ASSOCIATED NEUROTOXICITY SYNDROME

Cytokine release syndrome (CRS), including life-threatening or fatal reactions, can occur in patients receiving TALVEY. Initiate TALVEY treatment with step-up dosing to reduce the risk of CRS. Withhold TALVEY until CRS resolves or permanently discontinue based on severity [see Dosage and Administration (2.2, 2.5) , Warnings and Precautions (5.1)] .

Neurologic toxicity, including immune effector cell-associated neurotoxicity syndrome (ICANS), and serious and life threatening or fatal reactions, can occur with TALVEY. Monitor patients for signs and symptoms of neurologic toxicity including ICANS during treatment and treat promptly. Withhold or permanently discontinue TALVEY based on severity [see Dosage and Administration (2.5), Warnings and Precautions (5.2)] .

Because of the risk of CRS and neurologic toxicity, including ICANS, TALVEY is available only through a restricted program called the TECVAYLI and TALVEY Risk Evaluation and Mitigation Strategy (REMS) [see Warnings and Precautions (5.3)] .

1 INDICATIONS AND USAGE

TALVEY is indicated for the treatment of adult patients with relapsed or refractory multiple myeloma who have received at least four prior lines of therapy, including a proteasome inhibitor, an immunomodulatory agent and an anti-CD38 monoclonal antibody.

This indication is approved under accelerated approval based on response rate and durability of response [see Clinical Studies (14)]. Continued approval for this indication may be contingent upon verification and description of clinical benefit in a confirmatory trial(s).

2 DOSAGE AND ADMINISTRATION

2.1 Important Dosing Information

Administer TALVEY subcutaneously according to the step-up dosing schedule in Tables 1 and 2 to reduce the incidence and severity of cytokine release syndrome (CRS) [see Dosage and Administration (2.2)] .

Administer pretreatment medications prior to each dose of TALVEY in the step-up dosing schedule as recommended [see Dosage and Administration (2.2, 2.3)].

TALVEY should only be administered by a qualified healthcare professional with appropriate medical support to manage severe reactions such as CRS and neurologic toxicity including immune effector cell-associated neurotoxicity syndrome (ICANS) [see Warnings and Precautions (5.1, 5.2)] .

Due to the risk of CRS and neurologic toxicity, including ICANS, patients should be hospitalized for 48 hours after administration of all doses within the TALVEY step-up dosing schedule [see Dosage and Administration (2.5)and Warnings and Precautions (5.1, 5.2)] .

2.2 Recommended Dosage

For subcutaneous injection.

Administer pretreatment medications prior to each dose of TALVEY in the step-up dosing schedule [see Dosage and Administration (2.3)] .

Administer TALVEY subcutaneously on a weekly or biweekly (every 2 weeks) dosing schedule according to Table 1 or Table 2. Continue treatment until disease progression or unacceptable toxicity.

Table 1: TALVEY Weekly Dosing Schedule
Dosing schedule | Day | Dose [Based on actual body weight.]
Step-up dosing schedule | Day 1 | Step-up dose 1 | 0.01 mg/kg
Step-up dosing schedule | Day 4 [Dose may be administered between 2 to 4 days after the previous dose and may be given up to 7 days after the previous dose to allow for resolution of adverse reactions.] | Step-up dose 2 | 0.06 mg/kg
Step-up dosing schedule | Day 7 | First treatment dose | 0.4 mg/kg
Weekly dosing schedule | One week after first treatment dose and weekly thereafter [Maintain a minimum of 6 days between weekly doses.] | Subsequent treatment doses | 0.4 mg/kg once weekly

Table 2: TALVEY Biweekly (Every 2 Weeks) Dosing Schedule
Dosing schedule | Day | Dose [Based on actual body weight.]
Step-up dosing schedule | Day 1 | Step-up dose 1 | 0.01 mg/kg
Step-up dosing schedule | Day 4 [Dose may be administered between 2 to 4 days after the previous dose and may be given up to 7 days after the previous dose to allow for resolution of adverse reactions.] | Step-up dose 2 | 0.06 mg/kg
Step-up dosing schedule | Day 7 | Step-up dose 3 | 0.4 mg/kg
Step-up dosing schedule | Day 10 [Dose may be administered between 2 to 7 days after step-up dose 3.] | First treatment dose | 0.8 mg/kg
Biweekly (every 2 weeks) dosing schedule | Two weeks after first treatment dose and every 2 weeks thereafter [Maintain a minimum of 12 days between biweekly (every 2 weeks) doses.] | Subsequent treatment doses | 0.8 mg/kg every 2 weeks

2.3 Recommended Pretreatment Medications

Administer the following pretreatment medications 1 to 3 hours before each dose of TALVEY in the step-up dosing schedule to reduce the risk of CRS [see Warnings and Precautions (5.1)] .

- Corticosteroid (oral or intravenous dexamethasone, 16 mg or equivalent)
- Antihistamines (oral or intravenous diphenhydramine, 50 mg or equivalent)
- Antipyretics (oral or intravenous acetaminophen, 650 mg to 1,000 mg or equivalent)

Administration of pretreatment medications may be required for subsequent doses for patients who repeat doses within the TALVEY step-up dosing schedule due to dose delays (see Table 3or Table 4) or for patients who experienced CRS (see Table 5).

2.4 Dosage Delays

If a dose of TALVEY is delayed, restart therapy based on the recommendations in Table 3 and Table 4 and resume weekly or biweekly (every 2 weeks) dosing schedule accordingly [see Dosage and Administration (2.1)] ; if a dose is delayed by more than 28 days for an adverse reaction, evaluate the benefit-risk of restarting TALVEY. Administer pretreatment medications prior to restarting TALVEY and monitor patients following administration of TALVEY [see Dosage and Administration (2.2)].

Table 3: Recommendations for Restarting TALVEY after Dose Delay – Weekly Dosing Schedule
Last Dose Administered | Time from Last Dose Administered | TALVEY Recommendation [Administer pretreatment medications prior to restarting TALVEY. After restarting TALVEY, resume weekly dosing schedule accordingly [see Dosage and Administration (2.2)] .]
0.01 mg/kg | More than 7 days | Restart TALVEY step-up dosing schedule at step-up dose 1 (0.01 mg/kg).
0.06 mg/kg | 8 to 28 days | Repeat step-up dose 2 (0.06 mg/kg) and continue TALVEY step-up dosing schedule.
0.06 mg/kg | More than 28 days | Restart TALVEY step-up dosing schedule at step-up dose 1 (0.01 mg/kg).
0.4 mg/kg | 8 to 28 days | Continue TALVEY dosing schedule at treatment dose (0.4 mg/kg weekly).
0.4 mg/kg | 29 to 56 days | Restart TALVEY step-up dosing schedule at step-up dose 2 (0.06 mg/kg).
0.4 mg/kg | More than 56 days | Consider permanent discontinuation. If restarting TALVEY, begin with the step-up dosing schedule at step-up dose 1 (0.01 mg/kg).

Table 4: Recommendations for Restarting TALVEY after Dose Delay – Biweekly (Every 2 Weeks) Dosing Schedule
Last Dose Administered | Time from Last Dose Administered | TALVEY Recommendation [Administer pretreatment medications prior to restarting TALVEY. After restarting TALVEY, resume biweekly (every 2 weeks) dosing schedule accordingly [see Dosage and Administration (2.2)] .]
0.01 mg/kg | More than 7 days | Restart TALVEY step-up dosing schedule at step-up dose 1 (0.01 mg/kg).
0.06 mg/kg | 8 to 28 days | Repeat step-up dose 2 (0.06 mg/kg) and continue TALVEY step-up dosing schedule.
0.06 mg/kg | More than 28 days | Restart TALVEY step-up dosing schedule at step-up dose 1 (0.01 mg/kg).
0.4 mg/kg | 8 to 28 days | Repeat step-up dose 3 (0.4 mg/kg) and continue TALVEY step-up dosing schedule.
0.4 mg/kg | 29 to 56 days | Restart TALVEY step-up dosing schedule at step-up dose 2 (0.06 mg/kg).
0.4 mg/kg | More than 56 days | Consider permanent discontinuation. If restarting TALVEY, begin with the step-up dosing schedule at step-up dose 1 (0.01 mg/kg).
0.8 mg/kg | 15 to 28 days | Continue TALVEY dosing schedule at treatment dose (0.8 mg/kg every 2 weeks).
0.8 mg/kg | 29 to 56 days | Restart TALVEY step-up dosing schedule at step-up dose 3 (0.4 mg/kg).
0.8 mg/kg | More than 56 days | Consider permanent discontinuation. If restarting TALVEY, begin with the step-up dosing schedule at step-up dose 1 (0.01 mg/kg).

2.5 Dosage Modifications for Adverse Reactions

Dose delays may be required to manage toxicities related to TALVEY [see Warnings and Precautions (5)] .

See Table 5, Table 6, and Table 7for recommended actions for the management of CRS, ICANS, and neurologic toxicity. See Table 8for recommended dose modifications for other adverse reactions.

Cytokine Release Syndrome (CRS)

Identify CRS based on clinical presentation [see Warnings and Precautions (5.1)] . Evaluate and treat other causes of fever, hypoxia, and hypotension. If CRS is suspected, withhold TALVEY until CRS resolves or permanently discontinue based on severity, manage according to the recommendations in Table 5, consider further management per current practice guidelines. Administer supportive therapy for CRS, which may include intensive care for severe or life-threatening CRS. Consider laboratory testing to monitor for disseminated intravascular coagulation (DIC), hematology parameters, as well as pulmonary, cardiac, renal, and hepatic function.

Table 5: Recommendations for Management of CRS
CRS Grade [Based on American Society for Transplantation and Cellular Therapy (ASTCT) grading for CRS (Lee et al 2019).] | Presenting Symptoms | Actions
Grade 1 | Temperature ≥100.4°F (38°C) [Attributed to CRS. Fever may not always be present concurrently with hypotension or hypoxia as it may be masked by interventions such as antipyretics or anticytokine therapy (e.g., corticosteroids).] | - Withhold TALVEY until CRS resolves. [See Table 3 and Table 4 for recommendations on restarting TALVEY after dose delays for adverse reactions [see Dosage and Administration (2.4)].] - Administer pretreatment medication prior to next dose.
Grade 2 | Temperature ≥100.4°F (38°C) with either:; - Hypotension responsive to fluids and not requiring vasopressors, or - Oxygen requirement of low-flow nasal cannula [Low-flow nasal cannula is ≤6 L/min, and high-flow nasal cannula is >6 L/min.] or blow-by. | - Withhold TALVEY until CRS resolves. - Administer pretreatment medications prior to next dose. - Patients should be hospitalized for 48 hours following the next dose.
Grade 3 | Temperature ≥100.4°F (38°C) with either:; - Hypotension requiring one vasopressor, with or without vasopressin, or - Oxygen requirement of high-flow nasal cannula , facemask, non-rebreather mask, or Venturi mask | Duration less than 48 hours; - Withhold TALVEY until CRS resolves. - Provide supportive therapy, which may include intensive care. - Administer pretreatment medications prior to the next dose. - Patients should be hospitalized for 48 hours following the next dose.
Grade 3 | Temperature ≥100.4°F (38°C) with either:; - Hypotension requiring one vasopressor, with or without vasopressin, or - Oxygen requirement of high-flow nasal cannula , facemask, non-rebreather mask, or Venturi mask | Recurrent or duration greater than or equal to 48 hours; - Permanently discontinue TALVEY. - Provide supportive therapy, which may include intensive care.
Grade 4 | Temperature ≥100.4°F (38°C) with either:; - Hypotension requiring multiple vasopressors (excluding vasopressin). - Or, oxygen requirement of positive pressure (e.g., continuous positive airway pressure [CPAP], bilevel positive airway pressure [BiPAP], intubation, and mechanical ventilation) | - Permanently discontinue TALVEY. - Provide supportive therapy, which may include intensive care.

Neurologic Toxicity, including ICANS

At the first sign of neurologic toxicity, including ICANS, withhold TALVEY and consider neurology evaluation. Rule out other causes of neurologic symptoms. Provide supportive therapy, which may include intensive care, for severe or life-threatening neurologic toxicities, including ICANS [see Warnings and Precautions (5.2)] . Manage ICANS and neurologic toxicity according to the recommendations in Table 6 and Table 7 and consider further management per current practice guidelines.

Table 6: Recommendations for Management of ICANS
Grade [Based on ASTCT 2019 grading for ICANS.] | Presenting Symptoms [Management is determined by the most severe event, not attributable to any other cause.] | Actions
Grade 1 | ICE score 7–9 [If patient is arousable and able to perform Immune Effector Cell-Associated Encephalopathy (ICE) Assessment, assess: Orientation (oriented to year, month, city, hospital = 4 points); Naming (name 3 objects, e.g., point to clock, pen, button = 3 points); Following Commands (e.g., "show me 2 fingers" or "close your eyes and stick out your tongue" = 1 point); Writing (ability to write a standard sentence = 1 point; and Attention (count backwards from 100 by ten = 1 point). If patient is unarousable and unable to perform ICE Assessment (Grade 4 ICANS) = 0 points.] , or depressed level of consciousness [Attributable to no other cause.] : awakens spontaneously. | - Withhold TALVEY until ICANS resolves. [See Table 3 and Table 4 for recommendations on restarting TALVEY after dose delays for adverse reactions [see Dosage and Administration (2.4)].] - Monitor neurologic symptoms, and consider consultation with neurologist and other specialists for further evaluation and management. - Consider non-sedating, anti-seizure medicines (e.g., levetiracetam) for seizure prophylaxis.
Grade 2 | ICE score 3–6 , or depressed level of consciousness : awakens to voice. | - Withhold TALVEY until ICANS resolves. - Administer dexamethasone [All references to dexamethasone administration are dexamethasone or equivalent.] 10 mg intravenously every 6 hours. Continue dexamethasone use until resolution to Grade 1 or less, then taper. - Monitor neurologic symptoms and consider consultation with neurologist and other specialists for further evaluation and management. - Consider non-sedating, anti-seizure medicines (e.g., levetiracetam) for seizure prophylaxis. - Patients should be hospitalized for 48 hours following the next dose of TALVEY [see Dosage and Administration (2.1)] .
Grade 3 | ICE score 0–2 , (If ICE score is 0, but the patient is arousable (e.g., awake with global aphasia) and able to perform assessment) or depressed level of consciousness : awakens only to tactile stimulus, or seizures , either:; - any clinical seizure, focal or generalized, that resolves rapidly, or - non-convulsive seizures on electroencephalogram (EEG) that resolve with intervention,; or raised intracranial pressure: focal/local edema on neuroimaging . | First Occurrence of Grade 3 ICANS:; - Withhold TALVEY until ICANS resolves. - Administer dexamethasone 10 mg intravenously every 6 hours. Continue dexamethasone use until resolution to Grade 1 or less, then taper. - Monitor neurologic symptoms and consider consultation with neurologist and other specialists for further evaluation and management. - Consider non-sedating, anti-seizure medicines (e.g., levetiracetam) for seizure prophylaxis. - Provide supportive therapy, which may include intensive care. - Patients should be hospitalized for 48 hours following the next dose of TALVEY [see Dosage and Administration (2.1)] .; Recurrent Grade 3 ICANS:; - Permanently discontinue TALVEY. - Administer dexamethasone 10 mg intravenously and repeat dose every 6 hours. Continue dexamethasone use until resolution to Grade 1 or less, then taper. - Monitor neurologic symptoms and consider consultation with neurologist and other specialists for further evaluation and management. - Consider non-sedating, anti-seizure medicines (e.g., levetiracetam) for seizure prophylaxis. - Provide supportive therapy, which may include intensive care.
Grade 3 | ICE score 0–2 , (If ICE score is 0, but the patient is arousable (e.g., awake with global aphasia) and able to perform assessment) or depressed level of consciousness : awakens only to tactile stimulus, or seizures , either:; - any clinical seizure, focal or generalized, that resolves rapidly, or - non-convulsive seizures on electroencephalogram (EEG) that resolve with intervention,; or raised intracranial pressure: focal/local edema on neuroimaging .
Grade 4 | ICE score 0 (Patient is unarousable and unable to perform ICE assessment) or depressed level of consciousness : either:; - patient is unarousable or requires vigorous or repetitive tactile stimuli to arouse, or - stupor or coma,; or seizures , either:; - life-threatening prolonged seizure (>5 minutes), or - repetitive clinical or electrical seizures without return to baseline in between,; or motor findings :; - deep focal motor weakness such as hemiparesis or paraparesis,; or raised intracranial pressure/cerebral edema , with signs/symptoms such as:; - diffuse cerebral edema on neuroimaging, or - decerebrate or decorticate posturing, or - cranial nerve VI palsy, or - papilledema, or - Cushing's triad. | - Permanently discontinue TALVEY. - Administer dexamethasone 10 mg intravenously and repeat dose every 6 hours. Continue dexamethasone use until resolution to Grade 1 or less, then taper. - Alternatively, consider administration of methylprednisolone 1,000 mg per day intravenously and continue methylprednisolone 1,000 mg per day intravenously for 2 or more days. - Monitor neurologic symptoms and consider consultation with neurologist and other specialists for further evaluation and management. - Consider non-sedating, anti-seizure medicines (e.g., levetiracetam) for seizure prophylaxis. - Provide supportive therapy, which may include intensive care.

Table 7: Recommendations for Management of Neurologic Toxicity (excluding ICANS)
Adverse Reaction | Severity [Based on National Cancer Institute Common Terminology Criteria for Adverse Events (NCI CTCAE), version 4.03.] | Actions
Neurologic Toxicity (excluding ICANS) | Grade 1 | - Withhold TALVEY until neurologic toxicity symptoms resolve or stabilize. [See Table 3 and Table 4 for recommendations on restarting TALVEY after dose delays for adverse reactions [see Dosage and Administration (2.4)] .] [For ataxia/balance disorder, perform benefit risk assessment prior to resuming treatment with TALVEY.]
Neurologic Toxicity (excluding ICANS) | Grade 2 Grade 3 (First occurrence) | - Withhold TALVEY until neurologic toxicity symptoms improve to Grade 1 or less. - Provide supportive therapy.
Neurologic Toxicity (excluding ICANS) | Grade 3 (Recurrent) Grade 4 | - Permanently discontinue TALVEY. - Provide supportive therapy, which may include intensive care.

Other Adverse Reactions

The recommended dose modifications for other adverse reactions are provided in Table 8.

Table 8: Recommended Dose Modifications for Other Adverse Reactions
Adverse Reaction | Severity | Dose Modification
Oral Toxicity and Weight Loss [see Warnings and Precautions (5.4)] | Grade 1–2 | - Provide supportive care. - Consider withholding TALVEY if not responsive to supportive care. [See Table 3 and Table 4 for recommendations on restarting TALVEY after dose delays for adverse reactions [see Dosage and Administration (2.4)].]
Oral Toxicity and Weight Loss [see Warnings and Precautions (5.4)] | Grade 3 | - Withhold TALVEY until resolution to Grade 1 or better and provide supportive care.
Oral Toxicity and Weight Loss [see Warnings and Precautions (5.4)] | Grade 4 | - Permanently discontinue TALVEY.
Infections [see Warnings and Precautions (5.5)] | All Grades | - Withhold TALVEY in the step-up phase in patients until infection resolves.
Infections [see Warnings and Precautions (5.5)] | Grade 3 | - Withhold TALVEY during the treatment phase until infection improves to Grade 1 or better within 28 days. [For Grade 3 or 4 infection, if TALVEY is withheld for more than 28 days, restart step-up dosing when infection improves to Grade 1 or better.]
Infections [see Warnings and Precautions (5.5)] | Grade 4 | Consider permanent discontinuation of TALVEY.; - If TALVEY is not permanently discontinued, withhold subsequent treatment doses of TALVEY (i.e., doses administered after TALVEY step-up dosing schedule) until adverse reaction improves to Grade 1 or better.
Cytopenias [see Warnings and Precautions (5.6)] | Absolute neutrophil count less than 0.5 × 10^9/L | - Withhold TALVEY until absolute neutrophil count is 0.5 × 10^9/L or higher.
Cytopenias [see Warnings and Precautions (5.6)] | Febrile neutropenia | - Withhold TALVEY until absolute neutrophil count is 1 × 10^9/L or higher and fever resolves.
Cytopenias [see Warnings and Precautions (5.6)] | Hemoglobin less than 8 g/dL | - Withhold TALVEY until hemoglobin is 8 g/dL or higher.
Cytopenias [see Warnings and Precautions (5.6)] | Platelet count less than 25,000/mcL Platelet count between 25,000/mcL and 50,000/mcL with bleeding | - Withhold TALVEY until platelet count is 25,000/mcL or higher and no evidence of bleeding.
Skin Reactions [see Warnings and Precautions (5.7)] | Grade 3–4 | - Withhold TALVEY until adverse reaction improves to Grade 1 or baseline.
Other Non-hematologic Adverse Reactions [Based on National Cancer Institute Common Terminology Criteria for Adverse Events (NCI-CTCAE), Version 4.03.] [see Warnings and Precautions (5.8)and Adverse Reactions (6.1)] | Grade 3 | - Withhold TALVEY until adverse reaction improves to Grade 1 or baseline.
Other Non-hematologic Adverse Reactions [Based on National Cancer Institute Common Terminology Criteria for Adverse Events (NCI-CTCAE), Version 4.03.] [see Warnings and Precautions (5.8)and Adverse Reactions (6.1)] | Grade 4 | Consider permanent discontinuation of TALVEY.; - If TALVEY is not permanently discontinued, withhold subsequent treatment doses of TALVEY (i.e., doses administered after TALVEY step-up dosing schedule) until adverse reaction improves to Grade 1 or less.

2.6 Preparation and Administration

Administer TALVEY via subcutaneous injection by a healthcare provider.

TALVEY should be administered by a healthcare provider with adequate medical personnel and appropriate medical equipment to manage severe reactions, including CRS and neurologic toxicity, including ICANS [see Warnings and Precautions (5.1, 5.2)] .

TALVEY 3 mg/1.5 mL (2 mg/mL) vial and TALVEY 40 mg/mL vial are supplied as ready-to-use solution for injection that do not need dilution prior to administration.

Do not combine TALVEY vials of different concentrations to achieve treatment dose.

Use aseptic technique to prepare and administer TALVEY.

Preparation

Refer to the following reference tables for the preparation of TALVEY.

- Use Table 9 to determine total dose, injection volume, and number of vials required based on patient's actual body weight for the 0.01 mg/kg dose using TALVEY 3 mg/1.5 mL (2 mg/mL) vial.

Table 9: 0.01 mg/kg Dose: Injection Volumes using TALVEY 3 mg/1.5 mL (2 mg/mL) Vial
 | Body Weight (kg) | Total Dose (mg) | Volume of Injection (mL) | Number of Vials (1 vial = 1.5 mL)
0.01 mg/kg Dose | 35 to 39 | 0.38 | 0.19 | 1
0.01 mg/kg Dose | 40 to 45 | 0.42 | 0.21 | 1
0.01 mg/kg Dose | 46 to 55 | 0.5 | 0.25 | 1
0.01 mg/kg Dose | 56 to 65 | 0.6 | 0.3 | 1
0.01 mg/kg Dose | 66 to 75 | 0.7 | 0.35 | 1
0.01 mg/kg Dose | 76 to 85 | 0.8 | 0.4 | 1
0.01 mg/kg Dose | 86 to 95 | 0.9 | 0.45 | 1
0.01 mg/kg Dose | 96 to 105 | 1 | 0.5 | 1
0.01 mg/kg Dose | 106 to 115 | 1.1 | 0.55 | 1
0.01 mg/kg Dose | 116 to 125 | 1.2 | 0.6 | 1
0.01 mg/kg Dose | 126 to 135 | 1.3 | 0.65 | 1
0.01 mg/kg Dose | 136 to 145 | 1.4 | 0.7 | 1
0.01 mg/kg Dose | 146 to 155 | 1.5 | 0.75 | 1
 | 156 to 160 | 1.6 | 0.8 | 1

- Use Table 10 to determine total dose, injection volume, and number of vials required based on patient's actual body weight for the 0.06 mg/kg dose using TALVEY 3 mg/1.5 mL (2 mg/mL) vial.

Table 10: 0.06 mg/kg Dose: Injection Volumes using TALVEY 3 mg/1.5 mL (2 mg/mL) Vial
 | Body Weight (kg) | Total Dose (mg) | Volume of Injection (mL) | Number of Vials (1 vial = 1.5 mL)
0.06 mg/kg Dose | 35 to 39 | 2.2 | 1.1 | 1
0.06 mg/kg Dose | 40 to 45 | 2.6 | 1.3 | 1
0.06 mg/kg Dose | 46 to 55 | 3 | 1.5 | 1
0.06 mg/kg Dose | 56 to 65 | 3.6 | 1.8 | 2
0.06 mg/kg Dose | 66 to 75 | 4.2 | 2.1 | 2
0.06 mg/kg Dose | 76 to 85 | 4.8 | 2.4 | 2
0.06 mg/kg Dose | 86 to 95 | 5.4 | 2.7 | 2
0.06 mg/kg Dose | 96 to 105 | 6 | 3 | 2
0.06 mg/kg Dose | 106 to 115 | 6.6 | 3.3 | 3
0.06 mg/kg Dose | 116 to 125 | 7.2 | 3.6 | 3
0.06 mg/kg Dose | 126 to 135 | 7.8 | 3.9 | 3
0.06 mg/kg Dose | 136 to 145 | 8.4 | 4.2 | 3
0.06 mg/kg Dose | 146 to 155 | 9 | 4.5 | 3
 | 156 to 160 | 9.6 | 4.8 | 4

- Use Table 11 to determine total dose, injection volume, and number of vials required based on patient's actual body weight for the 0.4 mg/kg dose using TALVEY 40 mg/mL vial.

Table 11: 0.4 mg/kg Dose: Injection Volumes using TALVEY 40 mg/mL Vial
 | Body Weight (kg) | Total Dose (mg) | Volume of Injection (mL) | Number of Vials (1 vial = 1 mL)
0.4 mg/kg Dose | 35 to 39 | 14.8 | 0.37 | 1
0.4 mg/kg Dose | 40 to 45 | 16 | 0.4 | 1
0.4 mg/kg Dose | 46 to 55 | 20 | 0.5 | 1
0.4 mg/kg Dose | 56 to 65 | 24 | 0.6 | 1
0.4 mg/kg Dose | 66 to 75 | 28 | 0.7 | 1
0.4 mg/kg Dose | 76 to 85 | 32 | 0.8 | 1
0.4 mg/kg Dose | 86 to 95 | 36 | 0.9 | 1
0.4 mg/kg Dose | 96 to 105 | 40 | 1 | 1
0.4 mg/kg Dose | 106 to 115 | 44 | 1.1 | 2
0.4 mg/kg Dose | 116 to 125 | 48 | 1.2 | 2
0.4 mg/kg Dose | 126 to 135 | 52 | 1.3 | 2
0.4 mg/kg Dose | 136 to 145 | 56 | 1.4 | 2
0.4 mg/kg Dose | 146 to 155 | 60 | 1.5 | 2
 | 156 to 160 | 64 | 1.6 | 2

- Use Table 12 to determine total dose, injection volume, and number of vials required based on patient's actual body weight for the 0.8 mg/kg dose using TALVEY 40 mg/mL vial.

Table 12: 0.8 mg/kg Dose: Injection Volumes using TALVEY 40 mg/mL Vial
 | Body Weight (kg) | Total Dose (mg) | Volume of Injection (mL) | Number of Vials (1 vial = 1 mL)
0.8 mg/kg Dose | 35 to 39 | 29.6 | 0.74 | 1
0.8 mg/kg Dose | 40 to 45 | 34 | 0.85 | 1
0.8 mg/kg Dose | 46 to 55 | 40 | 1 | 1
0.8 mg/kg Dose | 56 to 65 | 48 | 1.2 | 2
0.8 mg/kg Dose | 66 to 75 | 56 | 1.4 | 2
0.8 mg/kg Dose | 76 to 85 | 64 | 1.6 | 2
0.8 mg/kg Dose | 86 to 95 | 72 | 1.8 | 2
0.8 mg/kg Dose | 96 to 105 | 80 | 2 | 2
0.8 mg/kg Dose | 106 to 115 | 88 | 2.2 | 3
0.8 mg/kg Dose | 116 to 125 | 96 | 2.4 | 3
0.8 mg/kg Dose | 126 to 135 | 104 | 2.6 | 3
0.8 mg/kg Dose | 136 to 145 | 112 | 2.8 | 3
0.8 mg/kg Dose | 146 to 155 | 120 | 3 | 3
 | 156 to 160 | 128 | 3.2 | 4

- Parenteral drug products should be inspected visually for particulate matter and discoloration prior to administration, whenever solution and container permit. Check that the TALVEY solution for injection is colorless to light yellow. Do not use if the solution is discolored, cloudy, or if foreign particles are present.
- Remove the appropriate strength TALVEY vial(s) from refrigerated storage [2°C to 8°C (36°F to 46°F)] and equilibrate to ambient temperature [15°C to 30°C (59°F to 86°F)] for at least 15 minutes. Do not warm TALVEY in any other way.
- Once equilibrated, gently swirl the vial for approximately 10 seconds to mix. Do not shake.
- Withdraw the required injection volume of TALVEY from the vial(s) into an appropriately sized syringe using a transfer needle.
  - Each injection volume should not exceed 2 mL. Divide doses requiring greater than 2 mL equally into multiple syringes.
- TALVEY is compatible with stainless steel injection needles and polypropylene or polycarbonate syringe material.
- Replace the transfer needle with an appropriately sized needle for injection.

Administration

- Inject the required volume of TALVEY into the subcutaneous tissue of the abdomen (preferred injection site). Alternatively, TALVEY may be injected into the subcutaneous tissue at other sites (e.g., thigh). If multiple injections are required, TALVEY injections should be at least 2 cm apart.
- Do not inject into tattoos or scars or areas where the skin is red, bruised, tender, hard or not intact.
- Any unused medicinal product or waste material should be disposed in accordance with local requirements.

Storage

The prepared syringes should be administered immediately. If immediate administration is not possible, store the TALVEY solution refrigerated at 2°C to 8°C (36°F to 46°F) for up to 24 hours followed by at room temperature of 15°C to 30°C (59°F to 86°F) for up to 24 hours. Discard if stored for more than 24 hours refrigerated or more than 24 hours at room temperature. If stored in the refrigerator, allow the solution to come to room temperature before administration.

3 DOSAGE FORMS AND STRENGTHS

Injection

- 3 mg/1.5 mL (2 mg/mL) colorless to light yellow solution in a single-dose vial
- 40 mg/mL colorless to light yellow solution in a single-dose vial

4 CONTRAINDICATIONS

None.

5 WARNINGS AND PRECAUTIONS

5.1 Cytokine Release Syndrome (CRS)

TALVEY can cause cytokine release syndrome, including life-threatening or fatal reactions [see Adverse Reactions (6.1)] .

In the clinical trial, CRS occurred in 76% of patients who received TALVEY at the recommended dosages, with Grade 1 CRS occurring in 57% of patients, Grade 2 in 17%, and Grade 3 in 1.5%. Recurrent CRS occurred in 30% of patients. Most events occurred following step-up dose 1 (29%) or step-up dose 2 (44%) at the recommended dosages. CRS occurred in 33% of patients with step-up dose 3 in the biweekly dosing schedule (N=153). CRS occurred in 30% of patients with the first 0.4 mg/kg treatment dose and in 12% of patients treated with the first 0.8 mg/kg treatment dose. The CRS rate for both dosing schedules combined was less than 3% for each of the remaining doses in Cycle 1 and less than 3% cumulatively from Cycle 2 onward. The median time to onset of CRS was 27 (range: 0.1 to 167) hours from the last dose, and the median duration was 17 (range: 0 to 622) hours. Clinical signs and symptoms of CRS include but are not limited to pyrexia, hypotension, chills, hypoxia, headache, and tachycardia. Potentially life-threatening complications of CRS may include cardiac dysfunction, acute respiratory distress syndrome, neurologic toxicity, renal and/or hepatic failure, and disseminated intravascular coagulation (DIC).

Initiate TALVEY therapy with step-up dosing and administer pre-treatment medications (corticosteroids, antihistamine, and antipyretics) prior to each dose of TALVEY in the step-up dosing schedule to reduce the risk of CRS. Monitor patients following administration accordingly. In patients who experience CRS, pre-treatment medications should be administered prior to the next TALVEY dose [see Dosage and Administration (2.2, 2.3)].

Counsel patients to seek medical attention should signs or symptoms of CRS occur. At the first sign of CRS, immediately evaluate patient for hospitalization and institute treatment with supportive care based on severity and consider further management per current practice guidelines. Withhold TALVEY until CRS resolves or permanently discontinue based on severity [see Dosage and Administration (2.5)] .

TALVEY is available only through a restricted program under a REMS [see Warnings and Precautions (5.3)] .

5.2 Neurologic Toxicity including ICANS

TALVEY can cause serious, life-threatening, or fatal neurologic toxicity, including ICANS [see Adverse Reactions (6.1)] .

In the clinical trial, neurologic toxicity, including ICANS, occurred in 55% of patients who received TALVEY at the recommended dosages, with Grade 3 or 4 neurologic toxicity occurring in 6% of patients. The most frequent neurologic toxicities were headache (20%), encephalopathy (15%), sensory neuropathy (14%), and motor dysfunction, including ataxia/cerebellar ataxia (10%). ICANS was reported in 9% of 265 patients where ICANS was collected and who received TALVEY at the recommended dosages [see Adverse Reactions (6.1)] . Recurrent ICANS occurred in 3% of patients. Most patients experienced ICANS following step-up dose 1 (3%), step-up dose 2 (3%), step-up dose 3 of the biweekly dosing schedule (1.8%), or the initial treatment dose of the weekly dosing schedule (2.6%) (N=156) or the biweekly dosing schedule (3.7%) (N=109). The median time to onset of ICANS was 2.5 (range: 1 to 16) days after the most recent dose with a median duration of 2 (range: 1 to 22) days. The onset of ICANS can be concurrent with CRS, following resolution of CRS, or in the absence of CRS. Clinical signs and symptoms of ICANS may include but are not limited to confusional state, depressed level of consciousness, disorientation, somnolence, lethargy, and bradyphrenia.

Monitor patients for signs and symptoms of neurologic toxicity during treatment. At the first sign of neurologic toxicity, including ICANS, immediately evaluate the patient and provide supportive care based on severity; withhold or permanently discontinue TALVEY based on severity and consider further management per current practice guidelines [see Dosage and Administration (2.5)].

Due to the potential for neurologic toxicity, patients receiving TALVEY are at risk of depressed level of consciousness. Advise patients to refrain from driving or operating heavy or potentially dangerous machinery during the step-up dosing schedule and for 48 hours after completion of the step-up dosing schedule [see Dosage and Administration (2.2)] and in the event of new onset of any neurological symptoms, until symptoms resolve.

TALVEY is available only through a restricted program under a REMS [see Warnings and Precautions (5.3)] .

5.3 TECVAYLI and TALVEY REMS

TALVEY is available only through a restricted program under a REMS called the TECVAYLI and TALVEY REMS because of the risks of CRS and neurologic toxicity, including ICANS [see Warnings and Precautions (5.1, 5.2)].

Notable requirements of the TECVAYLI and TALVEY REMS include the following:

- Prescribers must be certified with the program by enrolling and completing training.
- Prescribers must counsel patients receiving TALVEY about the risk of CRS and neurologic toxicity, including ICANS and provide patients with Patient Wallet Card.
- Pharmacies and healthcare settings that dispense TALVEY must be certified with the TECVAYLI and TALVEY REMS program and must verify prescribers are certified through the TECVAYLI and TALVEY REMS program.
- Wholesalers and distributers must only distribute TALVEY to certified pharmacies.

Further information about the TECVAYLI and TALVEY REMS program is available at www.TEC-TALREMS.com or by telephone at 1-855-810-8064.

5.4 Oral Toxicity and Weight Loss

TALVEY can cause oral toxicities, including dysgeusia, dry mouth, dysphagia, and stomatitis [see Adverse Reactions (6.1)] .

In the clinical trial, 80% of patients had oral toxicity, with Grade 3 occurring in 2.1% of patients who received TALVEY at the recommended dosages. The most frequent oral toxicities were dysgeusia (49%), dry mouth (34%), dysphagia (23%), and ageusia (18%). The median time to onset of oral toxicity was 15 (range: 1 to 634) days, and the median time to resolution to baseline was 43 (1 to 530) days. Oral toxicity did not resolve to baseline in 65% of patients.

TALVEY can cause weight loss [see Adverse Reactions (6.1)] . In the clinical trial, 62% of patients experienced weight loss, regardless of having an oral toxicity, including 29% of patients with Grade 2 (10% or greater) weight loss and 2.7% of patients with Grade 3 (20% or greater) weight loss. The median time to onset of Grade 2 or higher weight loss was 67 (range: 6 to 407) days, and the median time to resolution was 50 (range: 1 to 403) days. Weight loss did not resolve in 57% of patients who reported weight loss.

Monitor patients for signs and symptoms of oral toxicity. Counsel patients to seek medical attention should signs or symptoms of oral toxicity occur and provide supportive care as per current clinical practice including consultation with a nutritionist. Monitor weight regularly during therapy. Evaluate clinically significant weight loss further. Withhold TALVEY or permanently discontinue based on severity [see Dosage and Administration (2.5)] .

5.5 Infections

TALVEY can cause serious infections, including life-threatening or fatal infections [see Adverse Reactions (6.1)] .

In the clinical trial, serious infections occurred in 16% of patients, with fatal infections in 1.5% of patients. Grade 3 or 4 infections occurred in 17% of patients. The most common serious infections reported were bacterial infection (8%), which included sepsis, and COVID-19 (2.7%).

Monitor patients for signs and symptoms of infection prior to and during treatment with TALVEY and treat appropriately. Administer prophylactic antimicrobials according to local guidelines. Withhold or consider permanent discontinuation of TALVEY as recommended based on severity [see Dosage and Administration (2.5)] .

5.6 Cytopenias

TALVEY can cause cytopenias, including neutropenia and thrombocytopenia [see Adverse Reactions (6.1)] .

In the clinical trial, Grade 3 or 4 decreased neutrophils occurred in 35% of patients, and Grade 3 or 4 decreased platelets occurred in 22% of patients who received TALVEY. The median time to onset for Grade 3 or 4 neutropenia was 22 (range: 1 to 312) days, and the median time to resolution to Grade 2 or lower was 8 (range: 1 to 79) days. The median time to onset for Grade 3 or 4 thrombocytopenia was 12 (range: 2 to 183) days, and the median time to resolution to Grade 2 or lower was 10 (range: 1 to 64) days. Monitor complete blood counts during treatment and withhold TALVEY as recommended based on severity [see Dosage and Administration (2.5)] .

5.7 Skin Toxicity

TALVEY can cause serious skin reactions, including rash, maculo-papular rash, erythema, and erythematous rash [see Adverse Reactions (6.1)] .

In the clinical trial, skin reactions occurred in 62% of patients, with Grade 3 skin reactions in 0.3%. The median time to onset was 25 (range: 1 to 630) days. The median time to improvement to Grade 1 or less was 33 days.

Monitor for skin toxicity, including rash progression. Consider early intervention and treatment to manage skin toxicity. Withhold TALVEY as recommended based on severity [see Dosage and Administration (2.5)] .

5.8 Hepatotoxicity

TALVEY can cause hepatotoxicity. In the clinical trial, elevated ALT occurred in 33% of patients, with Grade 3 or 4 ALT elevation occurring in 2.7%; elevated AST occurred in 31% of patients, with Grade 3 or 4 AST elevation occurring in 3.3%. Grade 3 or 4 elevations of total bilirubin occurred in 0.3% of patients [see Adverse Reactions (6.1)] . Liver enzyme elevation can occur with or without concurrent CRS.

Monitor liver enzymes and bilirubin at baseline and during treatment as clinically indicated. Withhold TALVEY or consider permanent discontinuation of TALVEY based on severity [see Dosage and Administration (2.5)] .

5.9 Embryo-Fetal Toxicity

Based on its mechanism of action, TALVEY may cause fetal harm when administered to a pregnant woman. Advise pregnant women of the potential risk to the fetus. Advise females of reproductive potential to use effective contraception during treatment with TALVEY and for 3 months after the last dose [see Use in Specific Populations (8.1, 8.3)] .

6 ADVERSE REACTIONS

The following adverse reactions are also described elsewhere in the labeling:

- Cytokine Release Syndrome [see Warnings and Precautions (5.1)]
- Neurologic Toxicity, including ICANS [see Warnings and Precautions (5.2)]
- Oral Toxicity and Weight Loss [see Warnings and Precautions (5.4)]
- Infections [see Warnings and Precautions (5.5)]
- Cytopenias [see Warnings and Precautions (5.6)]
- Skin Toxicity [see Warnings and Precautions (5.7)]
- Hepatotoxicity [see Warnings and Precautions (5.8)]

6.1 Clinical Trials Experience

Because clinical trials are conducted under widely varying conditions, adverse reaction rates observed in the clinical trials of a drug cannot be directly compared to rates in the clinical trials of another drug and may not reflect the rates observed in practice.

Relapsed/Refractory Multiple Myeloma

MonumenTAL-1

The safety of TALVEY was evaluated in 339 adult patients with relapsed or refractory multiple myeloma. Patients treated with the weekly dosing schedule received step-up doses of 0.01 mg/kg and 0.06 mg/kg of TALVEY followed by TALVEY 0.4 mg/kg subcutaneously weekly thereafter. Patients treated with the biweekly (every 2 weeks) dosing schedule received step-up doses of 0.01 mg/kg, 0.06 mg/kg, and 0.3 mg/kg (0.75 times the recommended step-up dose 3) followed by TALVEY 0.8 mg/kg subcutaneously every 2 weeks thereafter. The duration of exposure for the 0.4 mg/kg weekly regimen was 5.9 (range: 0.0 to 25.3) months (N=186) and for the 0.8 mg/kg biweekly (every 2 weeks) regimen, it was 3.7 (range: 0.0 to 17.9) months (N=153).

Serious adverse reactions occurred in 47% of patients who received TALVEY. Serious adverse reactions in ≥ 2% of patients included CRS (13%), bacterial infection (8%) including sepsis, pyrexia (4.7%), ICANS (3.8%), COVID-19 (2.7%), neutropenia (2.1%), and upper respiratory tract infection (2.1%).

Fatal adverse reactions occurred in 3.2% of patients who received TALVEY, including COVID -19 (0.6%), dyspnea (0.6%), general physical health deterioration (0.6%), bacterial infection (0.3%) including sepsis, basilar artery occlusion (0.3%), fungal infection (0.3%), infection (0.3%), and pulmonary embolism (0.3%).

Permanent discontinuation of TALVEY due to an adverse reaction occurred in 9% of patients. Adverse reactions which resulted in permanent discontinuation of TALVEY in > 1% of patients included ICANS.

Dosage interruptions of TALVEY due to an adverse reaction occurred in 56% of patients. Adverse reactions which required dosage interruption in > 5% of patients included pyrexia (15%), CRS (12%), upper respiratory tract infection (9%), COVID-19 (9%), bacterial infection (7%) including sepsis, neutropenia (6%), and rash (6%).

The most common adverse reactions (≥ 20%) were pyrexia, CRS, dysgeusia, nail disorder, musculoskeletal pain, skin disorder, rash, fatigue, weight decreased, dry mouth, xerosis, dysphagia, upper respiratory tract infection, diarrhea, hypotension, and headache. The most common Grade 3 or 4 laboratory abnormalities (≥ 30%) were lymphocyte count decreased, neutrophil count decreased, white blood cell decreased, and hemoglobin decreased.

Table 13 summarizes the adverse reactions in MonumenTAL-1.

Table 13: Adverse Reactions (≥10%) in Patients with Relapsed or Refractory Multiple Myeloma Who Received TALVEY in MonumenTAL-1
 | TALVEY N=339
System Organ Class Adverse Reaction | Any Grade (%) | Grade 3 or 4 (%)
General disorders and administration site conditions
Pyrexia [Includes other related terms.] | 83 | 4.7 [Only grade 3 adverse reactions occurred.]
Fatigue | 37 | 3.5
Chills | 19 | 0
Pain | 18 | 1.8
Edema | 14 | 0
Injection site reaction | 13 | 0
Immune system disorders
Cytokine release syndrome | 76 | 1.5
Gastrointestinal disorders
Dysgeusia [Dysgeusia: ageusia, dysgeusia, hypogeusia and taste disorder.] [Per CTCAE v4.03, maximum toxicity grade for dysgeusia is 2 and maximum toxicity grade for dry mouth is 3.] | 70 | 0
Dry mouth | 34 | 0
Dysphagia | 23 | 0.9
Diarrhea | 21 | 0.9
Stomatitis [Stomatitis: cheilitis, glossitis, glossodynia, mouth ulceration, oral discomfort, oral mucosal erythema, oral pain, stomatitis, swollen tongue, tongue discomfort, tongue erythema, tongue edema and tongue ulceration.] | 18 | 1.2
Nausea | 18 | 0
Constipation | 16 | 0
Oral disorder [Oral disorder: oral disorder, oral dysesthesia, oral mucosal exfoliation, oral toxicity and oropharyngeal pain.] | 12 | 0
Skin and subcutaneous tissue disorders
Nail disorder [Nail disorder: koilonychia, nail bed disorder, nail cuticle fissure, nail discoloration, nail disorder, nail dystrophy, nail hypertrophy, nail pitting, nail ridging, nail toxicity, onychoclasis, onycholysis and onychomadesis.] | 50 | 0
Skin disorder [Skin disorder: palmar-plantar erythrodysesthesia syndrome, palmoplantar keratoderma, skin discoloration, skin exfoliation and skin fissures.] | 41 | 0.3
Rash [Rash: dermatitis, dermatitis acneiform, dermatitis contact, dermatitis exfoliative, dermatitis exfoliative generalized, erythema, exfoliative rash, rash, rash erythematous, rash macular, rash maculo-papular, rash papular, rash pruritic, rash pustular, rash vesicular and stasis dermatitis.] | 38 | 3.5
Xerosis [Xerosis: dry eye, dry skin and xerosis.] | 30 | 0
Pruritus | 19 | 0.3
Musculoskeletal and connective tissue disorders
Musculoskeletal pain | 43 | 3.2
Investigations
Weight decreased | 35 | 1.5
Infections and infestations
Upper respiratory tract infection | 22 | 2.7
Bacterial infection including sepsis [Bacterial infection including sepsis: bacteremia, bacterial prostatitis, carbuncle, cellulitis, citrobacter infection, clostridium difficile colitis, clostridium difficile infection, cystitis escherichia, cystitis klebsiella, diverticulitis, enterobacter bacteremia, escherichia pyelonephritis, escherichia sepsis, folliculitis, gastroenteritis escherichia coli, helicobacter gastritis, human ehrlichiosis, klebsiella bacteremia, klebsiella sepsis, moraxella infection, otitis media acute, pitted keratolysis, pneumococcal sepsis, pneumonia, pneumonia streptococcal, pseudomonal bacteremia, pyuria, renal abscess, salmonella sepsis, sepsis, septic shock, skin infection, staphylococcal bacteremia, staphylococcal infection, staphylococcal sepsis, streptococcal bacteremia, tooth abscess, tooth infection, urinary tract infection enterococcal, and urinary tract infection pseudomonal.] [Includes fatal outcome(s): COVID-19 (N=2), dyspnea (N=2), bacterial infection including sepsis (N=1), fungal infection (N=1).] | 19 | 9
COVID-19 | 11 | 2.7
Fungal infection [Fungal infection: body tinea, candida infection, ear infection fungal, esophageal candidiasis, fungal infection, fungal sepsis, fungal skin infection, genital candidiasis, onychomycosis, oral candidiasis, oral fungal infection, oropharyngeal candidiasis, tinea pedis, vulvovaginal candidiasis, and vulvovaginal mycotic infection.] | 10 | 0.6
Vascular disorders
Hypotension | 21 | 2.9
Nervous system disorders
Headache | 21 | 0.6
Encephalopathy [Encephalopathy: agitation, altered state of consciousness, amnesia, aphasia, bradyphrenia, confusional state, delirium, depressed level of consciousness, disorientation, encephalopathy, hallucination, lethargy, memory impairment, mood altered, restlessness, sleep disorder and somnolence.] | 15 | 1.8
Sensory neuropathy [Sensory neuropathy: dysesthesia, hyperesthesia, hypoesthesia, hypoesthesia oral, immune-mediated neuropathy, neuralgia, neuropathy peripheral, paresthesia, peripheral sensory neuropathy, polyneuropathy, sciatica and vestibular neuronitis.] | 14 | 0
Motor dysfunction [Motor dysfunction: dysarthria, dysgraphia, dysmetria, dysphonia, gait disturbance, muscle atrophy, muscle spasms, muscular weakness and tremor.] | 10 | 0.6
Metabolism and nutrition disorders
Decreased appetite | 19 | 1.2
Respiratory, thoracic and mediastinal disorders
Cough | 17 | 0
Dyspnea | 11 | 1.8
Hypoxia | 10 | 1.5
Cardiac disorders
Tachycardia | 11 | 0.6
Adverse reactions were graded based on CTCAE Version 4.03, with the exception of CRS, which was graded per ASTCT 2019 criteria.

Clinically relevant adverse reactions reported in <10% of patients who received TALVEY included ICANS and viral infection.

Table 14 summarizes select laboratory abnormalities in MonumenTAL-1.

Table 14: Select Laboratory Abnormalities (≥30%) That Worsened from Baseline in Patients with Relapsed or Refractory Multiple Myeloma Who Received TALVEY in MonumenTAL-1
 | TALVEY [The denominator used to calculate the rate varied from 326 to 338 based on the number of patients with a baseline value and at least one post-treatment value.]
Laboratory Abnormality | Any Grade (%) | Grade 3 or 4 (%)
Hematology
Lymphocyte count decreased | 90 | 80
White blood cell decreased | 73 | 35
Hemoglobin decreased | 67 | 30
Neutrophil count decreased | 64 | 35
Platelet count decreased | 62 | 22
Chemistry
Albumin decreased | 66 | 2.1
Alkaline phosphatase increased | 49 | 1.5
Phosphate decreased | 44 | 13
Gamma-glutamyl transferase increased | 38 | 7
Alanine aminotransferase increased | 33 | 2.7
Potassium decreased | 31 | 4.4
Sodium decreased | 31 | 6
Aspartate aminotransferase increased | 31 | 3.3
Laboratory toxicity grades are derived based on the NCI CTCAE (National Cancer Institute Common Terminology Criteria for Adverse Events) Version 4.03.

7 DRUG INTERACTIONS

For certain cytochrome P450 (CYP) substrates, minimal changes in the substrate concentration may lead to serious adverse reactions. Monitor for toxicity or drug concentrations of such CYP substrates when co-administered with TALVEY.

Talquetamab-tgvs causes release of cytokines [see Clinical Pharmacology (12.2)] that may suppress activity of CYP enzymes, resulting in increased exposure of CYP substrates. Increased exposure of CYP substrates is more likely to occur from initiation of the TALVEY step-up dosing schedule up to 14 days after the first treatment dose and during and after CRS [see Warnings and Precautions (5.1)] .

8 USE IN SPECIFIC POPULATIONS

8.1 Pregnancy

Risk Summary

Based on the mechanism of action, TALVEY may cause fetal harm when administered to a pregnant woman [see Clinical Pharmacology (12.1)] . There are no available data on the use of TALVEY in pregnant women to evaluate for a drug associated risk. No animal reproductive or developmental toxicity studies have been conducted with talquetamab-tgvs.

Talquetamab-tgvs causes T-cell activation and cytokine release; immune activation may compromise pregnancy maintenance. Human immunoglobulin G (IgG) is known to cross the placenta; therefore, TALVEY has the potential to be transmitted from the mother to the developing fetus. Advise women of the potential risk to the fetus.

In the U.S. general population, the estimated background risk of major birth defects and miscarriage in clinically recognized pregnancies is 2% to 4% and 15% to 20%, respectively.

8.2 Lactation

Risk Summary

There is no information regarding the presence of talquetamab-tgvs in human milk, the effect on the breastfed child, or the effect on milk production. Maternal IgG is known to be present in human milk. The effects of local gastrointestinal exposure and limited systemic exposure in the breastfed child to TALVEY are unknown. Because of the potential for serious adverse reactions in a breastfed child, advise women not to breastfeed during treatment with TALVEY and for 3 months after the last dose.

8.3 Females and Males of Reproductive Potential

TALVEY may cause fetal harm when administered to a pregnant woman [see Use in Specific Populations (8.1)] .

Pregnancy Testing

Verify pregnancy status of females of reproductive potential prior to initiating TALVEY.

Contraception

Females

Advise females of reproductive potential to use effective contraception during treatment with TALVEY and for 3 months after the last dose.

8.4 Pediatric Use

The safety and efficacy of TALVEY have not been established in pediatric patients.

8.5 Geriatric Use

There were 339 patients in the clinical trial for relapsed or refractory multiple myeloma. Of the total number of TALVEY-treated patients in the study, 178 (53%) patients were 65 years of age and older, while 57 (17%) patients were 75 years of age and older. No overall differences in safety or effectiveness were observed in patients 65 to less than 74 years of age compared to younger patients. There was a higher rate of fatal adverse reactions in patients 75 years of age or older compared to younger patients [see Adverse Reactions (6.1)]. Clinical studies did not include sufficient numbers of patients 75 years of age or over to determine whether they respond differently from younger patients.

11 DESCRIPTION

Talquetamab-tgvs is a bispecific GPRC5D-directed CD3 T-cell engager. It is a humanized IgG4 proline, alanine, alanine (IgG4-PAA)-based bispecific antibody produced by Chinese hamster ovary (CHO) cells using recombinant DNA technology. Talquetamab-tgvs consists of an anti-GPRC5D heavy chain and light chain and an anti-CD3 heavy chain and light chain with two interchain disulfide bonds connecting the two arms. The molecular weight of talquetamab-tgvs is 147 kDa.

TALVEY®(talquetamab-tgvs) injection is a sterile, preservative-free colorless to light yellow solution supplied in a single-dose vial for subcutaneous administration.

Each TALVEY 1.5 mL single-dose vial contains 3 mg of talquetamab-tgvs, edetate disodium (0.027 mg), glacial acetic acid (0.36 mg), polysorbate 20 (0.6 mg), sodium acetate (1.39 mg), sucrose (120 mg), and Water for Injection, USP. The pH is 5.2.

Each TALVEY 1 mL single-dose vial contains 40 mg of talquetamab-tgvs, edetate disodium (0.018 mg), glacial acetic acid (0.24 mg), polysorbate 20 (0.4 mg), sodium acetate (0.90 mg), sucrose (80 mg), and Water for Injection, USP. The pH is 5.2.

12 CLINICAL PHARMACOLOGY

12.1 Mechanism of Action

Talquetamab-tgvs is a bispecific T-cell engaging antibody that binds to the CD3 receptor expressed on the surface of T-cells and G protein-coupled receptor class C group 5 member D (GPRC5D) expressed on the surface of multiple myeloma cells and non-malignant plasma cells, as well as healthy tissues such as epithelial cells in keratinized tissues of the skin and tongue.

In vitro, talquetamab-tgvs activated T-cells caused the release of proinflammatory cytokines and resulted in the lysis of multiple myeloma cells. Talquetamab-tgvs had anti-tumor activity in mouse models of multiple myeloma.

12.2 Pharmacodynamics

Serum concentrations of cytokines (IL-6, IL-10, TNF-α, and IFN-γ) and IL-2R were measured before and after administration of each step-up dose, the first three treatment doses at 0.4 mg/kg once weekly, and the first two treatment doses at 0.8 mg/kg every two weeks. Increased concentrations of IL-6, IL-10, and IL-2R were observed during this period.

Higher talquetamab-tgvs exposures (i.e., AUC and Cmax) are associated with higher incidence of some adverse reactions (including oral toxicity, nail toxicity, and skin reactions). The exposure-response relationships for effectiveness and the time course of pharmacodynamic response of talquetamab-tgvs have not been fully characterized.

12.3 Pharmacokinetics

The Cmaxand AUCtauof talquetamab-tgvs after subcutaneous administration increased proportionally over a dose range of 0.005 to 0.8 mg/kg weekly (0.01 to 2 times the recommended 0.4 mg/kg weekly treatment dose) and 0.8 to 1.2 mg/kg every two weeks (1 to 1.5 times the recommended 0.8 mg/kg every 2 weeks treatment dose). Ninety percent of steady state exposure was achieved 16 weeks after the first treatment dose for both regimens.

The Cmax, Ctrough, Cavg, and accumulation ratios of talquetamab-tgvs are presented in Table 15.

Table 15: Pharmacokinetic Parameters of Talquetamab-tgvs Following the Dose at 16 Weeks After the First Treatment Dose for the Approved Recommended Subcutaneous Dosages in Patients with Relapsed or Refractory Multiple Myeloma
 | Talquetamab-tgvs Dosage
Parameter | 0.4 mg/kg every week | 0.8 mg/kg every 2 weeks
Exposure [Data are presented as geometric mean (coefficient of variation %).]
Cmax(ng/mL) | 2,940 (67%) | 3,410 (63%)
Ctrough(ng/mL) | 2,410 (83%) | 1,930 (103%)
Cavg(ng/mL) | 2,730 (71%) | 2,770 (72%)
Accumulation Ratio [For the 0.4 mg/kg every week regimen, accumulation ratios are presented as the arithmetic mean of the 17 th treatment dose / the first treatment dose. For the 0.8 mg/kg every 2 weeks regimen, accumulation ratios are presented as the arithmetic mean of the 9 th treatment dose / the first treatment dose.]
Cmax | 4.4 | 1.8
Ctrough | 4.6 | 2.3
Cavg | 5.1 | 2.0
Cavg= Average concentration over the dosing interval; :Cmax= Maximum serum talquetamab-tgvs concentration; Ctrough= Serum talquetamab-tgvs concentration prior to next dose

Absorption

The geometric mean (coefficient of variation [CV] %) bioavailability of talquetamab-tgvs was 59% (22%) when administered subcutaneously.

The median (range) Tmaxof talquetamab-tgvs after the first and 17thtreatment dose of 0.4 mg/kg weekly were 3.7 (0.9 to 7) days and 2.5 (0.9 to 5.9) days, respectively.

The median (range) Tmaxof talquetamab-tgvs after the first and 9thtreatment dose of 0.8 mg/kg every 2 weeks were 3.4 (0.8 to 14) days and 3.6 (1 to 7.7) days, respectively.

Distribution

The geometric mean (CV%) volume of distribution of talquetamab-tgvs was 10.1 L (25%).

Elimination

Talquetamab-tgvs clearance decreases over time, with a mean (CV%) maximal reduction from the first treatment dose to 16 weeks after the first treatment dose of 40% (56%). The geometric mean (CV%) clearance is 0.90 L/day (63%) at 16 weeks after the first treatment dose. The mean (CV%) terminal half-life was 8.4 (41%) days after the first treatment dose and 12.2 (49%) days at 16 weeks after the first treatment dose.

Metabolism

Talquetamab-tgvs is expected to be metabolized into small peptides by catabolic pathways.

Specific Populations

The volume of distribution and clearance of talquetamab-tgvs increased with increasing bodyweight (40 kg to 143 kg).

There were no clinically significant differences in the pharmacokinetics of talquetamab-tgvs based on age (33 to 86 years), sex, race (White, Black or African American), ethnicity (Not Hispanic/Latino, Hispanic/Latino), mild or moderate renal impairment (creatinine clearance [CLcr] by Cockcroft-Gault equation: 30 to 89 mL/min) or mild (total bilirubin less than or equal to upper limit of normal [ULN] with AST greater than ULN or total bilirubin greater than 1 to 1.5 times ULN with any AST) or moderate (total bilirubin greater than 1.5 to less than 3 times ULN with any AST) hepatic impairment. The effects of severe renal impairment (CLcr less than 30 mL/min) or severe hepatic impairment (total bilirubin greater than 3 times ULN with any AST) on the pharmacokinetics of talquetamab-tgvs are unknown.

12.6 Immunogenicity

The observed incidence of anti-drug antibodies is highly dependent on the sensitivity and specificity of the assay. Differences in assay methods preclude meaningful comparisons of the incidence of anti-drug antibodies in the studies described below with the incidence of anti-drug antibodies in other studies, including those of talquetamab-tgvs or of other talquetamab products.

During treatment in MonumenTAL-1 (up to 25 months), 45/177 (25%) patients treated with subcutaneous TALVEY 0.4 mg/kg weekly (median follow-up 5.7 months) and 24/130 (18%) patients treated with subcutaneous TALVEY 0.8 mg/kg every 2 weeks (median follow-up 3.1 months) developed anti-talquetamab-tgvs antibodies. There was no identified clinically significant effect of anti-talquetamab-tgvs antibodies on the pharmacokinetics, pharmacodynamics, safety, or effectiveness of TALVEY.

13 NONCLINICAL TOXICOLOGY

13.1 Carcinogenesis, Mutagenesis, Impairment of Fertility

No carcinogenicity or genotoxicity studies have been conducted with talquetamab-tgvs.

No studies have been conducted to evaluate the effects of talquetamab-tgvs on fertility.

14 CLINICAL STUDIES

The efficacy of TALVEY monotherapy was evaluated in patients with relapsed or refractory multiple myeloma in a single-arm, open-label, multicenter study, MMY1001 (MonumenTAL-1) (NCT03399799, NCT04634552). The study included patients who had previously received at least three prior systemic therapies, including a proteasome inhibitor, an immunomodulatory agent, and an anti-CD38 monoclonal antibody. The study excluded patients who experienced T-cell redirection therapy within 3 months, prior Grade 3 or higher CRS related to any T-cell redirection therapy, an autologous stem cell transplant within the past 12 weeks, an allogeneic stem cell transplant within the past 6 months, Eastern Cooperative Oncology Group (ECOG) performance score of 3 or higher, stroke or seizure within the past 6 months, CNS involvement or clinical signs of meningeal involvement of multiple myeloma, and plasma cell leukemia, active or documented history of autoimmune disease (exception of vitiligo, resolved childhood atopic dermatitis, resolved Grave's Disease that is euthyroid based on clinical and laboratory testing).

Patients treated with the weekly dosing schedule received step-up doses of 0.01 mg/kg and 0.06 mg/kg of TALVEY followed by TALVEY 0.4 mg/kg subcutaneously weekly thereafter.

Patients treated with the biweekly (every 2 weeks) dosing schedule received step-up doses of 0.01 mg/kg, 0.06 mg/kg, and 0.3 mg/kg (0.75 times the recommended step-up dose 3) of TALVEY followed by TALVEY 0.8 mg/kg subcutaneously biweekly, thereafter. Patients on both dosing schedules were treated until disease progression or unacceptable toxicity.

The efficacy results from the 187 patients treated with TALVEY who were not exposed to prior T cell redirection therapy and who had received at least 4 prior lines of therapy are presented below; of these patients, the median age was 67 (range: 38 to 86) years, 57% were male, 90% were White, 5% were Black or African American, 3% were Asian, and 8% were Hispanic. Patients had received a median of 5 (range: 4 to 13) prior lines of therapy, and 78% had received prior autologous stem cell transplantation (ASCT). Ninety-four percent (94%) of patients were refractory to their last therapy, and 73% were refractory to a proteasome inhibitor, immunomodulatory agent, and anti-CD38 antibody. The International Staging System (ISS) at study entry was Stage I in 44%, Stage II in 34%, and Stage III in 22% of patients. High-risk cytogenetic factors (presence of t(4:14), t(14:16), and/or del(17p)) were present in 29% of patients; baseline cytogenetic data were not available in 11% of patients. Twenty-two percent (22%) of patients had extramedullary plasmacytomas.

Efficacy was based on overall response rate (ORR) and duration of response (DOR) as assessed by an Independent Review Committee using IMWG criteria. The median duration of follow-up from first response among responders receiving TALVEY 0.4 mg/kg weekly was 13.8 (range: 0.8 to 15.4) months.

Table 16: Efficacy Results for MMY1001 (MonumenTAL-1) in Patients Receiving 0.4 mg/kg Weekly TALVEY
 | 0.4 mg/kg Weekly (N=100)
Overall response rate (ORR=sCR+CR+VGPR+PR) | 73 (73%)
95% CI | (63.2%, 81.4%)
Stringent complete response (sCR) | 26%
Complete response (CR) | 9%
Very good partial response (VGPR) | 22%
Partial response (PR) | 16%
Duration of Response (DOR)
Median DOR (95% CI) (months) | 9.5 (6.5, NE)
CI=confidence interval; NE=not estimable

The median duration of follow-up from first response among responders receiving TALVEY 0.8 mg/kg biweekly was 5.9 (range: 0 to 9.5) months; an estimated 85% of responders maintained response for at least 9 months.

Table 17: Efficacy Results for MMY1001 (MonumenTAL-1) in Patients Receiving 0.8 mg/kg Biweekly (Every 2 Weeks) TALVEY
 | 0.8 mg/kg Biweekly (Every 2 Weeks) (N=87)
Overall response rate (ORR=sCR+CR+VGPR+PR) | 65 (73.6%)
95% CI | (63.0%, 82.4%)
Stringent complete response (sCR) | 20%
Complete response (CR) | 13%
Very good partial response (VGPR) | 25%
Partial response (PR) | 16%
Duration of Response (DOR)
Median DOR (95% CI) (months) | NE
CI=confidence interval; NE=not estimable

The median time to first response was 1.2 (range: 0.2 to 10.9) months and 1.3 (range: 0.2 to 9.2) months for 0.4 mg/kg weekly and 0.8 mg/kg biweekly (every 2 weeks), respectively.

Thirty-two patients were exposed to prior T cell redirection therapy and had received at least 4 prior lines of therapy, including a proteasome inhibitor, an immunomodulatory agent, and an anti-CD38 monoclonal antibody received TALVEY at the 0.4 mg/kg weekly dose. Patients had received a median of 6 (range: 4 to 15) prior therapies, with 81% exposed to CAR-T cell therapy and 25% exposed to a bispecific antibody. Ninety-four percent of patients were exposed to prior T cell redirection therapy directed at BCMA. The ORR per IRC assessment was 72% (95% CI: 53%, 86%). With a median duration of follow-up of 10.4 months, an estimated 59% of responders maintained response for at least 9 months.

16 HOW SUPPLIED/STORAGE AND HANDLING

TALVEY®(talquetamab-tgvs) injection is a sterile, preservative-free, colorless to light yellow solution supplied as follows:

- One 3 mg/1.5 mL (2 mg/mL) single-dose vial in a carton: NDC: 57894-469-01
- One 40 mg/mL single-dose vial in a carton: NDC: 57894-470-01

STORAGE AND HANDLING

Store refrigerated at 2°C to 8°C (36°F to 46°F) in original carton to protect from light.

Do not freeze.

17 PATIENT COUNSELING INFORMATION

Advise the patient to read the FDA-approved patient labeling (Medication Guide).

Cytokine Release Syndrome (CRS)

Discuss the signs and symptoms associated with CRS including, but not limited to, pyrexia, hypotension, chills, hypoxia, headache, and tachycardia. Counsel patients to seek medical attention should signs or symptoms of CRS occur. Advise patients that they should be hospitalized for 48 hours after administration of all doses within the TALVEY step-up dosing schedule [see Dosage and Administration (2.1, 2.5), Warnings and Precautions (5.1)] .

Neurologic Toxicity, including ICANS

Discuss the signs and symptoms associated with neurologic toxicity, including headache, encephalopathy, sensory neuropathy, difficulty speaking and understanding speech, difficulty with coordination, uncontrolled fast eye movement, motor dysfunction including ataxia/cerebellar ataxia, and symptoms of ICANS including confusional state, depressed level of consciousness, disorientation, somnolence, lethargy, and bradyphrenia. Counsel patients to seek medical attention should signs or symptoms of neurologic toxicity occur. Advise patients to refrain from driving or operating heavy or potentially dangerous machinery during the step-up dosing schedule and for 48 hours after completion of the step-up dosing schedule and in the event of new onset of any neurologic toxicity symptoms, until symptoms resolve [see Dosage and Administration (2.2, 2.5), Warnings and Precautions (5.2)].

TECVAYLI and TALVEY REMS

TALVEY is available only through a restricted program called the TECVAYLI and TALVEY REMS. Inform patients that they will be given a Patient Wallet Card that they should carry with them at all times and show to all of their healthcare providers. This card describes signs and symptoms of CRS and neurologic toxicity, including ICANS which, if experienced, should prompt the patient to immediately seek medical attention [see Warnings and Precautions (5.3)].

Oral Toxicity and Weight Loss

Discuss the signs and symptoms of oral toxicities including dysgeusia, dry mouth, dysphagia, and stomatitis. Counsel patients to seek medical attention should signs or symptoms of oral toxicity occur. Advise patients that they may experience weight loss and to report weight loss. Advise patients that they may be referred to a nutritionist for consultation [see Dosage and Administration (2.5), Warnings and Precautions (5.4)] .

Infections

Discuss the signs and symptoms of serious infections [see Dosage and Administration (2.5), Warnings and Precautions (5.5)] .

Cytopenias

Discuss the signs and symptoms associated with neutropenia and thrombocytopenia [see Dosage and Administration (2.5), Warnings and Precautions (5.6)] .

Skin Toxicity

Discuss the signs and symptoms of skin reactions [see Dosage and Administration (2.5), Warnings and Precautions (5.7)] .

Hepatotoxicity

Advise patients that liver enzyme elevations may occur and that they should report symptoms that may indicate liver toxicity, including fatigue, anorexia, right upper abdominal discomfort, dark urine, or jaundice [see Warnings and Precautions (5.8)].

Embryo-Fetal Toxicity

Advise pregnant women and females of reproductive potential of the potential risk to a fetus. Advise females of reproductive potential to inform their healthcare provider if they are pregnant or become pregnant. Advise females of reproductive potential to use effective contraception during treatment with TALVEY and for 3 months after the last dose [see Warnings and Precautions (5.9), Use in Specific Populations (8.1, 8.3)] .

Lactation

Advise women not to breastfeed during treatment with TALVEY and for 3 months after the last dose [see Use in Specific Populations (8.2)] .

Manufactured by:
Janssen Biotech, Inc.
Horsham, PA 19044, USA
U.S. License Number 1864

For patent information: www.janssenpatents.com

© 2023 Janssen Pharmaceutical Companies

MEDICATION GUIDE
TALVEY®[tal vay]
(talquetamab-tgvs) injection, for subcutaneous use

What is the most important information I should know about TALVEY?
TALVEY may cause side effects that are serious, life-threatening, or lead to death, including Cytokine Release Syndrome (CRS) and neurologic problems.
Call your healthcare provider or get medical help right away if you develop any of the signs or symptoms of CRS or neurologic problems listed below at any time during your treatment with TALVEY:
Cytokine Release Syndrome (CRS).CRS is common during treatment with TALVEY and can also be serious, life-threatening, or lead to death. Signs and symptoms of CRS may include:

- fever (100.4°F or higher)
- dizziness or lightheadedness
- chills
- difficulty breathing

- feeling anxious
- headache
- fast heartbeat

Neurologic problems.Symptoms of neurologic problems with TALVEY may include:

- headache
- feeling confused
- being less alert or aware
- feeling disoriented
- trouble speaking or writing
- shaking (tremors)
- numbness and tingling (feeling like "pins and needles")
- problems with walking, or loss of balance or coordination

- feeling sleepy
- feeling very sleepy with low energy
- slow or difficulty thinking
- seizures
- muscle weakness
- memory loss
- burning, throbbing, or stabbing pain
- fast eye movements that you cannot control

- Due to the risk of CRS and neurologic problems, you should be hospitalized for 48 hours after all doses of TALVEY that are part of the "step-up dosing schedule". The "step-up dosing schedule" is when you receive the first 2 or 3 doses of TALVEY, which are smaller "step-up" doses, and also the first full "treatment dose" of TALVEY.
- TALVEY is given weekly or every 2 weeks. Your healthcare provider will decide the number of days to wait between your doses of TALVEY as well as how many treatments you will receive.
  - If you receive TALVEY weekly, "Step-up dose 1" is given on day 1 of treatment. "Step-up dose 2" is usually given on day 4 of treatment. The first "treatment dose" is usually given on day 7 of treatment.
  - If you receive TALVEY every 2 weeks, "Step-up dose 1" is given on day 1 of treatment. "Step-up dose 2" is usually given on day 4 of treatment. "Step-up dose 3" is usually given on day 7 of treatment. The first "treatment dose" is usually given on day 10 of treatment.

- If your dose of TALVEY is delayed for any reason, you may need to repeat the "step-up dosing schedule" to receive TALVEY.
- Before each "step up" dose of TALVEY, you will receive medicines to help reduce your risk of CRS. Your healthcare provider will decide if you need to receive medicines to help reduce your risk of CRS with future doses.
- Your healthcare provider will monitor you for signs and symptoms of CRS, neurologic problems, as well as other side effects and treat you as needed.

TALVEY is available only through the TECVAYLI and TALVEY Risk Evaluation and Mitigation Strategy (REMS) due to the risk of CRS and neurologic problems.
You will receive a Patient Wallet Card from your healthcare provider. Carry the Patient Wallet Card with you at all times and show it to all of your healthcare providers.The Patient Wallet Card lists signs and symptoms of CRS and neurologic problems.
Get medical help right away if you develop any of the signs and symptoms listed on the Patient Wallet Card.You may need to be treated in a hospital.

- If you have any questions about TALVEY, ask your healthcare provider.
- Your healthcare provider may temporarily stop or completely stop your treatment with TALVEY if you develop CRS, neurologic problems or any other side effects that are severe.

See " What are the possible side effects of TALVEY?" for more information about side effects.

What is TALVEY?
TALVEY is a prescription medicine used to treat adults with multiple myeloma who:

- have already received at least 4 treatment regimens, including a proteasome inhibitor, an immunomodulatory agent and an anti-CD38 monoclonal antibody to treat their multiple myeloma, and
- their cancer has come back or did not respond to prior treatment.

It is not known if TALVEY is safe and effective in children.

Before you receive TALVEY, tell your healthcare provider about all of your medical conditions, including if you:

- have an infection
- are pregnant or plan to become pregnant. TALVEY may harm your unborn baby. Tell your healthcare provider if you become pregnant or think that you may be pregnant during treatment with TALVEY.
  Females who are able to become pregnant:
  - Your healthcare provider should do a pregnancy test before you start treatment with TALVEY.
  - You should use effective birth control (contraception) during treatment and for 3 months after your last dose of TALVEY.
- are breastfeeding or plan to breastfeed. It is not known if TALVEY passes into your breast milk. Do not breastfeed during treatment and for 3 months after your last dose of TALVEY.

Tell your healthcare provider about all the medicines you take,including prescription and over-the-counter medicines, vitamins, and herbal supplements.

How will I receive TALVEY?

- TALVEY will be given to you by your healthcare provider as an injection under your skin (subcutaneous injection), usually in the stomach area (abdomen). TALVEY may also be injected into your thigh or another area of your body.
- See " What is the most important information I should know about TALVEY?" at the beginning of this Medication Guide for information about how you will receive TALVEY.
- If you miss any appointments, call your healthcare provider as soon as possible to reschedule your appointment.

What should I avoid while receiving TALVEY?
Do notdrive, operate heavy machinery, or do other dangerous activities during and for 48 hours after your TALVEY "step-up dose" is completed or at any time during treatment with TALVEY, if you develop dizziness, confusion, tremors, sleepiness, or any other symptoms of neurologic problems until your symptoms go away.
See " What is the most important information I should know about TALVEY?" for more information about signs and symptoms of CRS and neurologic problems.

What are the possible side effects of TALVEY?
TALVEY may cause serious side effects, including:

- See " What is the most important information I should know about TALVEY?"
- Mouth problems and weight loss.Tell your healthcare provider or get medical help right away if you develop any of the following symptoms of mouth problems:

- changes in sense of taste
- dry mouth

- trouble swallowing
- mouth sores

Your healthcare provider will monitor you for these symptoms and will monitor your weight during treatment with TALVEY. Tell your healthcare provider if you lose weight during treatment with TALVEY.

- Infections. TALVEY can cause serious infections that can be life-threatening and may lead to death. Your healthcare provider will monitor you for signs and symptoms of infection before and during treatment with TALVEY. Tell your healthcare provider right away if you get develop any signs or symptoms of infection during treatment with TALVEY, including:

- fever of 100.4°F (38°C) or higher
- chills
- cough
- chest pain
- tiredness

- shortness of breath
- painful rash
- sore throat
- pain during urination
- feeling weak or generally unwell

- Decreased blood cell counts.Decreased blood cell counts are common during treatment with TALVEY and can also be severe. Your healthcare provider will check your blood cell counts during treatment with TALVEY. Tell your healthcare provider if you get any symptoms of infection or unusual bleeding or bruising.
- Skin problems. Skin problems are common during treatment with TALVEY and can also be serious. Tell your healthcare provider if you get skin problems such as skin rash, raised red bumps, or redness of the skin.
- Liver problems.Abnormal liver tests can happen during treatment with TALVEY. Your healthcare provider will do blood tests before and during treatment with TALVEY to check your liver. Tell your healthcare provider if you develop any of the following symptoms of liver problems:

- tiredness
- loss of appetite
- pain in your right upper stomach-area (abdomen)

- dark urine
- yellowing of your skin or the white part of your eyes

The most common side effects of TALVEY include:

- fever
- changes in your sense of taste
- nail problems
- muscle or joint pain
- rash
- feeling very tired
- weight loss
- dry mouth

- very dry skin that may affect the mucous membranes (such as the mouth and eyes)
- difficulty swallowing
- infected nose, sinuses or throat (cold)
- diarrhea
- low blood pressure
- headache

The most common severe abnormal lab test results with TALVEY include: decreased white blood cells and red blood cells. These are not all the possible side effects of TALVEY.
Call your doctor for medical advice about side effects. You may report side effects to FDA at 1-800-FDA-1088.

General Information about the safe and effective use of TALVEY.
Medicines are sometimes prescribed for purposes other than those listed in a Medication Guide. You can ask your pharmacist or healthcare provider for information about TALVEY that is written for health professionals.

What are the ingredients of TALVEY?
Active ingredient: talquetamab-tgvs
Inactive ingredients: edetate disodium, glacial acetic acid, polysorbate 20, sodium acetate, sucrose, and Water for Injection.
Manufactured by: Janssen Biotech, Inc., Horsham, PA 19044, USA
U.S. License Number 1864
© 2023 Janssen Pharmaceutical Companies
For patent information: www.janssenpatents.com
For more information, go to www.TALVEY.com or call 1-800-526-7736.

This Medication Guide has been approved by the U.S. Food and Drug Administration.

Revised: 10/2025

PRINCIPAL DISPLAY PANEL - 3 mg Vial Carton

NDC 57894-469-01

One Vial
Rx only

Talvey™
(talquetamab-tgvs)
Injection

3 mg/1.5 mL
(2 mg/mL)

Vials of different concentrations
should not be combined to
achieve treatment dose.

For subcutaneous injection by a
healthcare provider only.

Attention: Dispense the enclosed
Medication Guide to each patient.

Single-dose vial
Discard unused portion.

janssen

PRINCIPAL DISPLAY PANEL - 40 mg Vial Carton

NDC 57894-470-01

One Vial
Rx only

Talvey™
(talquetamab-tgvs)
Injection

40 mg/mL

Vials of different concentrations
should not be combined to
achieve treatment dose.

For subcutaneous injection
by a healthcare provider only.

Attention: Dispense the enclosed
Medication Guide to each patient.

Single-dose vial
Discard unused portion.

janssen